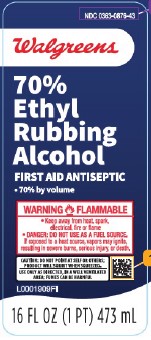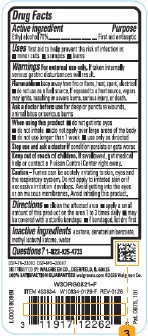 DRUG LABEL: Ethyl Rubbing Alcohol
NDC: 0363-0876 | Form: LIQUID
Manufacturer: Walgreen Co.
Category: otc | Type: HUMAN OTC DRUG LABEL
Date: 20260210

ACTIVE INGREDIENTS: ALCOHOL 70 mL/100 mL
INACTIVE INGREDIENTS: ACETONE; DENATONIUM BENZOATE; METHYL ISOBUTYL KETONE; WATER

Walgreens 876.002/876AC
70% Ethyl Rubbing Alcohol

Active Ingredient

Ethyl alcohol 70%

Purpose

First aid antiseptic

Uses

first aid to help prevent the risk of infection in:

- minor cuts
- scrapes
- burns

Warnings

For external use only. If taken internally serious gastric disturbances will result.

Flammable.

- Keep away from fire or flame, heat, spark, electrical
- do not use as a fuel source. If exposed to a heat source, vapors may ignite, resulting in severe burns, serious injury, or death.

Ask a doctor before use

for deep or puncture wounds, animal bites or serious burns

When using this product

- do not get into eyes
- do not inhale
- do not apply over large areas of the body
- do not use longer than 1 week
- use only as directed

Stop use and ask a doctor if

condition persists or gets worse

Keep out of reach of children.

If swallowed, get medical help or contact a Poison Control Center right away.

Caution

Fumes can be acutely irritating to skin, eyes and the respiratory system. Do not apply to irritated skin or if excessive irritation develops. Avoid getting into the eyes or on mucous membranes. Avoid inhaling this product.

Directions

- clean the affected area
- apply a small amount of this product on the affected area 1 to 3 times daily
- may be covered with a sterile bandage
- if bandaged, let dry first

Inactive ingredients

acetone, denatonium benzoate, methyl isobutyl ketone, water

Questions?

1-822-925-4733

Adverse reaction

DSP-TN-21091 DSP-MO-20087

Distributed by: Walgreen Co., Deerfield, IL 60015

100% Satisfaction Guaranteed walgreens.com ©2026 Walgreen Co.

Pat. D675,101

Principal display panel

NDC 0363-0876-43

Walgreens

70% Ethyl Rubbing Alcohol

First Aid Antseptic

- 70% by volume

WARNING FLAMMABLE

- Keep away from heat, spark, electrical, fire or flame
- DANGER: DO NOT USE AS A FUEL SOURCE.

If exposed to a heat source, vapors may ignite, resulting in severe burns, serious injury, or death.

CAUTION: Do not point at self or others; product will squirt when squeezed.

Use only as directed, in well-ventilated area; fumes can be harmful

16 FL OZ (1 PT) 473 mL